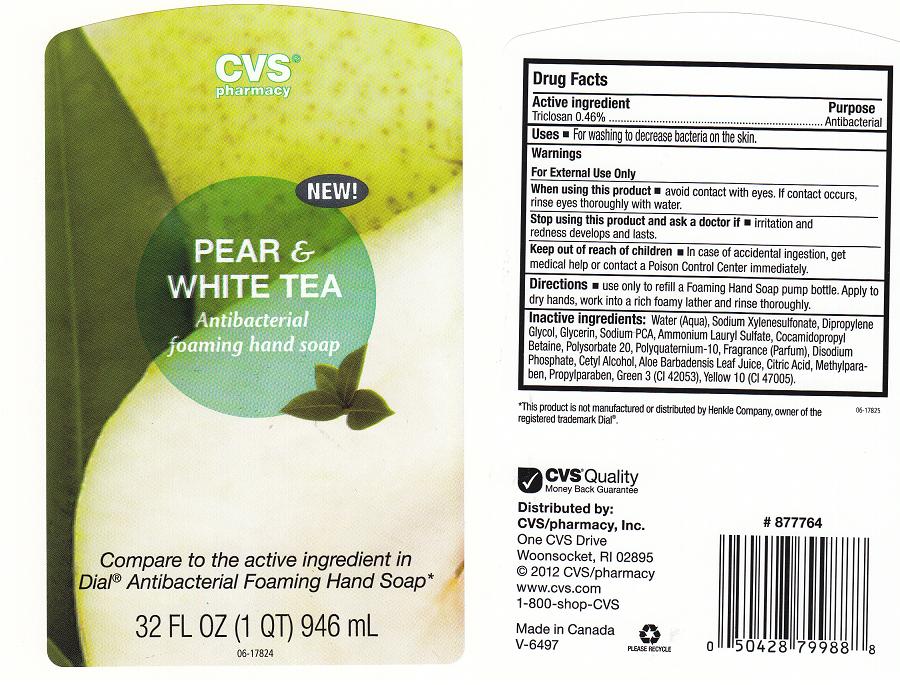 DRUG LABEL: CVS PHARMACY
NDC: 59779-188 | Form: LIQUID
Manufacturer: CVS PHARMACY
Category: otc | Type: HUMAN OTC DRUG LABEL
Date: 20120130

ACTIVE INGREDIENTS: TRICLOSAN 0.46 mL/100 mL
INACTIVE INGREDIENTS: WATER; SODIUM XYLENESULFONATE; DIPROPYLENE GLYCOL; GLYCERIN; SODIUM PYRROLIDONE CARBOXYLATE; AMMONIUM LAURYL SULFATE; COCAMIDOPROPYL BETAINE; POLYSORBATE 20; POLYQUATERNIUM-10 (400 CPS AT 2%); SODIUM PHOSPHATE, DIBASIC, ANHYDROUS; C12-16 ALCOHOLS; ALOE VERA LEAF; ANHYDROUS CITRIC ACID; METHYLPARABEN; PROPYLPARABEN; FD&C GREEN NO. 3; D&C YELLOW NO. 10

DRUG FACTS

ACTIVE INGREDIENT

TRICLOSAN 0.46%

PURPOSE

ANTIBACTERIAL

USES

FOR WASHING TO DECREASE BACTERIA ON THE SKIN

WARNINGS

FOR EXTERNAL USE ONLY

WHEN USING THIS PRODUCT

AVOID CONTACT WITH EYES. IF CONTACT OCCURS, RINSE EYES THOROUGHLY WITH WATER.

STOP USE AND ASK A DOCTOR

IRRITATION OR REDNESS DEVELOPS AND LASTS

KEEP OUT OF REACH OF CHILDREN

IN CASE OF ACCIDENTAL INGESTION, GET MEDICAL HELP OR CONTACT A POISON CONTROL CENTER IMMEDIATELY.

DIRECTIONS

APPLY A SMALL AMOUNT TO DRY HANDS. WORK INTO A RICH LATHER AND RINSE CLEAN

INACTIVE INGREDIENTS

WATER (AQUA), SODIUM XYLENE SULFONATE, DIPROPYLENE GLYCOL, GLYCERIN, SODIUM PCA, AMMONIUM LAURYL SULFATE, COCAMIDOPROPYL BETAINE, POLYSORBATE 20, POLYQUATERNIUM-10, FRAGRANCE (PARFUM), DISODIUM PHOSPHATE, CETYL ALCOHOL, ALOE BARBADENSIS LEAF JUICE, CITRIC ACID, METHYLPARABEN, PROPYLPARABEN, GREEN 3 (CI 42053), YELLOW 10 (CI 47005)